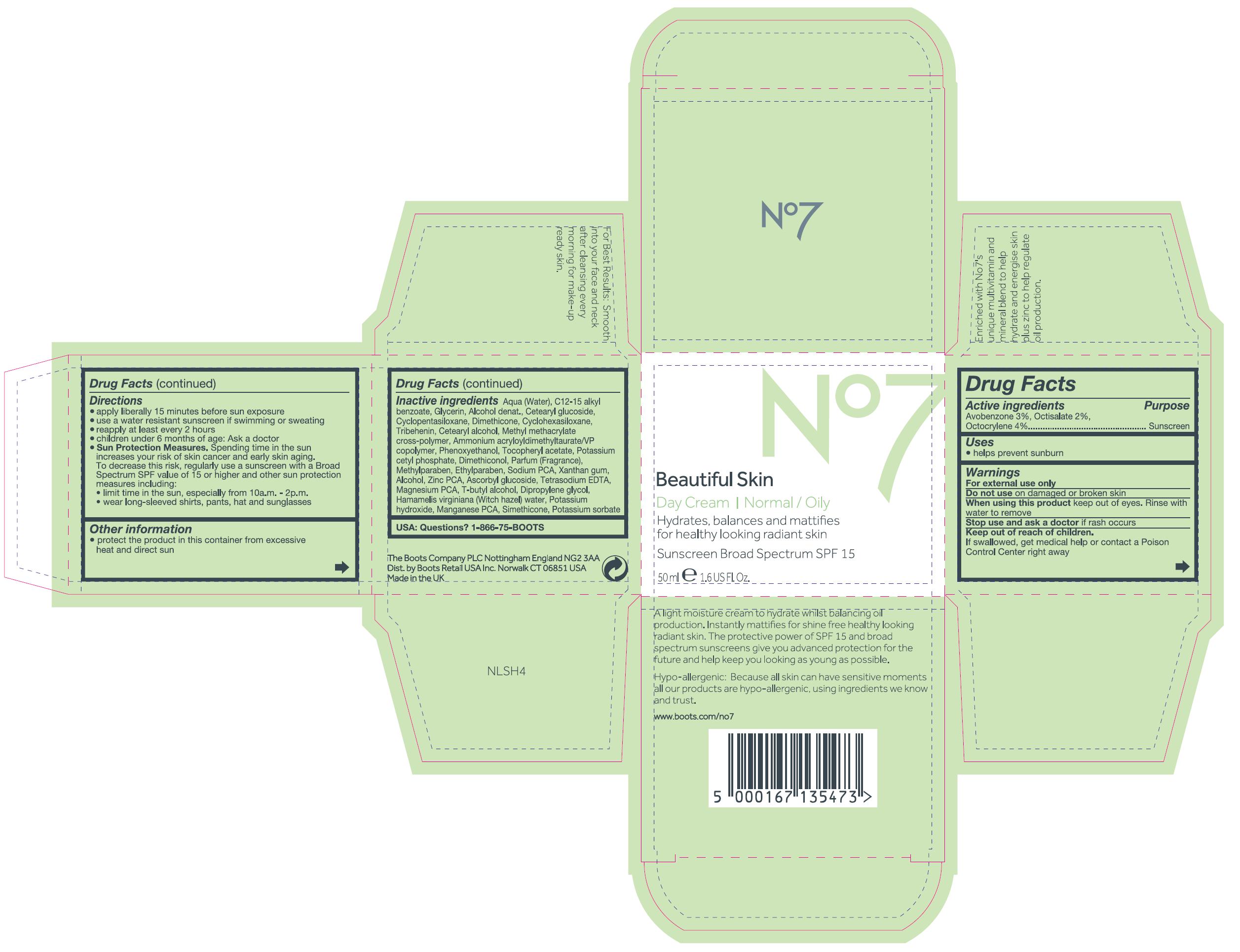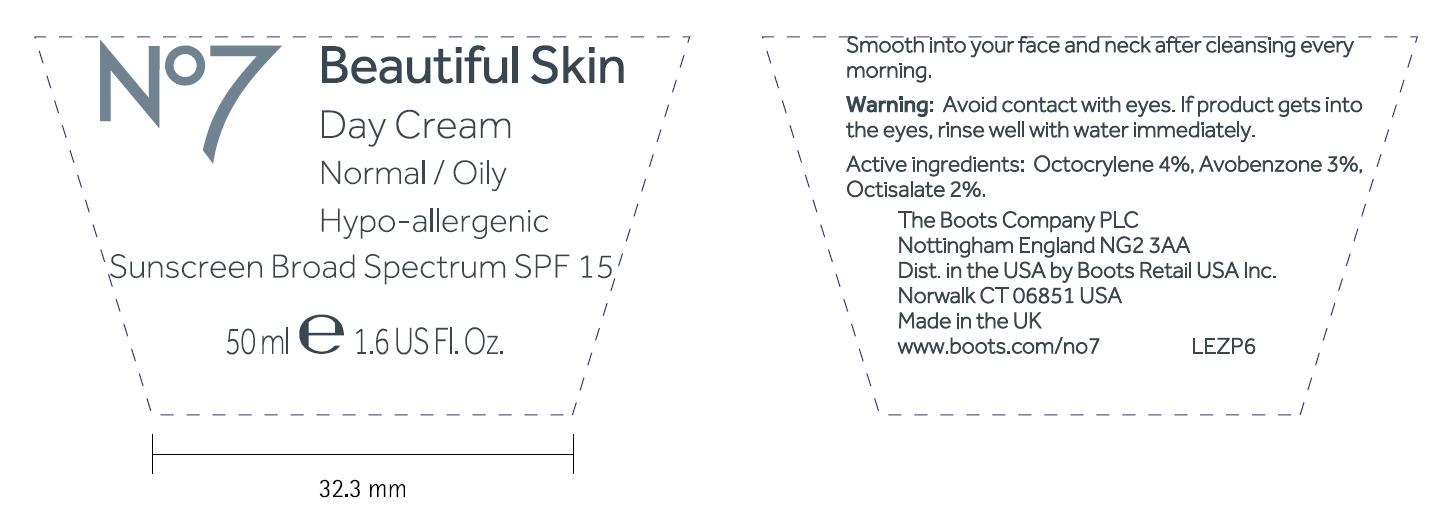 DRUG LABEL: No7 Beautiful Skin Day Normal Oily Sunscreen Broad Spectrum SPF 15
NDC: 11489-070 | Form: CREAM
Manufacturer: BCM Ltd
Category: otc | Type: HUMAN OTC DRUG LABEL
Date: 20200226

ACTIVE INGREDIENTS: Avobenzone 1.5 mg/50 mL; Octisalate 1 mg/50 mL; Octocrylene 2 mg/50 mL
INACTIVE INGREDIENTS: Water; ALKYL (C12-15) BENZOATE; GLYCERIN; Alcohol; CETEARYL GLUCOSIDE; CYCLOMETHICONE 5; Dimethicone; CYCLOMETHICONE 6; TRIBEHENIN; CETOSTEARYL ALCOHOL; AMMONIUM ACRYLOYLDIMETHYLTAURATE/VP COPOLYMER; PHENOXYETHANOL; .ALPHA.-TOCOPHEROL ACETATE; POTASSIUM CETYL PHOSPHATE; METHYLPARABEN; ETHYLPARABEN; SODIUM PYRROLIDONE CARBOXYLATE; XANTHAN GUM; ZINC PIDOLATE; ASCORBYL GLUCOSIDE; EDETATE SODIUM; MAGNESIUM PIDOLATE; TERT-BUTYL ALCOHOL; DIPROPYLENE GLYCOL; HAMAMELIS VIRGINIANA TOP WATER; POTASSIUM HYDROXIDE; POTASSIUM SORBATE

No7 Beautiful Skin Day Cream Normal Oily Sunscreen Broad Spectrum SPF 15

Inactive Ingredients

Aqua (water), C12-15 alkyl benzoate, Glycerin, Alcohol denat., Cetearyl glucoside, Cyclopentasiloxane, Dimethicone, Cyclohexasiloxane, Tribehenin, Cetearyl alcohol, Methyl methacrylate cross-polymer, Ammonium acryloyldimethyltaurate/VP copolymer, Phenoxyethanol, Tocopheryl acetate, Potassium cetyl phosphate, Dimethiconol, Parfum (Fragrance), Methylparaben, Ethylparaben, Sodium PCA, Xanthan gum, Alcohol, Zinc PCA, Ascorbyl glucoside, Tetrasodium EDTA, Magnesium PCA, T-butyl alcohol, Dipropylene glycol, Hamamelis virginiana (Witch hazel) water, Potassium hydroxide, Manganese PCA, Simethicone, Potassium sorbate

USA: Questions? 1-866-75-BOOTS

The Boots Company PLC Nottingham England NG2 3AA

Dist. by Boots Retail USA Inc. Norwalk CT 06851 USA

Made in the UK

DESCRIPTION

A light moisture cream to hydrate whilst balancing oil production. Instantly mattifies for shine free healthy looking radiant skin. The protective power of SPF 15 and broad spectrum sunscreens give you advanced protection for the future and and help keep you looking as young as possible.

Hypo-allergenic: Because all skin can have sensitive moments all our products are hypo-allergenic, using ingredients we know and trust.

www.boots.com/no7

DESCRIPTION

For Best Results: Smooth into your face and neck after cleansing every morning for make-up ready skin.

Enriched with No7's unique multivitamin and mineral blend to help hydrate and energise skin plus zinc to help regulate oil production.

Active Ingredients

Avobenzone 3%, Octisalate 2%, Octocrylene 4%

Purpose

Sunscreen

Uses

Helps prevent sunburn

Warnings

For external use only

Do not use on damaged or broken skin

When using this product keep out of eyes. Rinse with water to remove.

Stop use and ask a doctor if rash occurs

Keep out of reach of children.

If swallowed, get medical help or contact a Poison Control Center right away

Directions

Apply liberally 15 minutes before sun exposure

Use a water resistant sunscreen if swimming or sweating

Reapply at least every 2 hours

Children under 6 months of age: ask a doctor

Sun Protection Measures. Spending time in the sun increases your risk of skin cancer and early skin aging. To decrease this risk, regularly use a sunscreen with a broad spectrum SPF value of 15 or higher and other sun protection measures including:

limit time in the sun, especially from 10a.m. - 2p.m.

wear long-sleeved shirts, pants, hat and sunglasses

Other Information

Protect the product in this container from excessive heat and direct sun

INSTRUCTIONS FOR USE

JAR TEXT

Smooth into your face and neck after cleansing every morning

WARNINGS

JAR TEXT

Warning: Avoid contact with eyes. If product gets into the eyes, rinse well with water immediately.

ACTIVE INGREDIENT

JAR TEXT

Active ingredients: Octocrylene 4%, Avobenzone 3%, Octisalate 2%.

PATIENT COUNSELING INFORMATION

JAR TEXT

The Boots Company PLC

Nottingham England NG2 3AA

Dist. in the USA by Boots Retail USA Inc.

Norwalk CT 06851 USA

Made in the UK

www.boots.com/no7

Carton